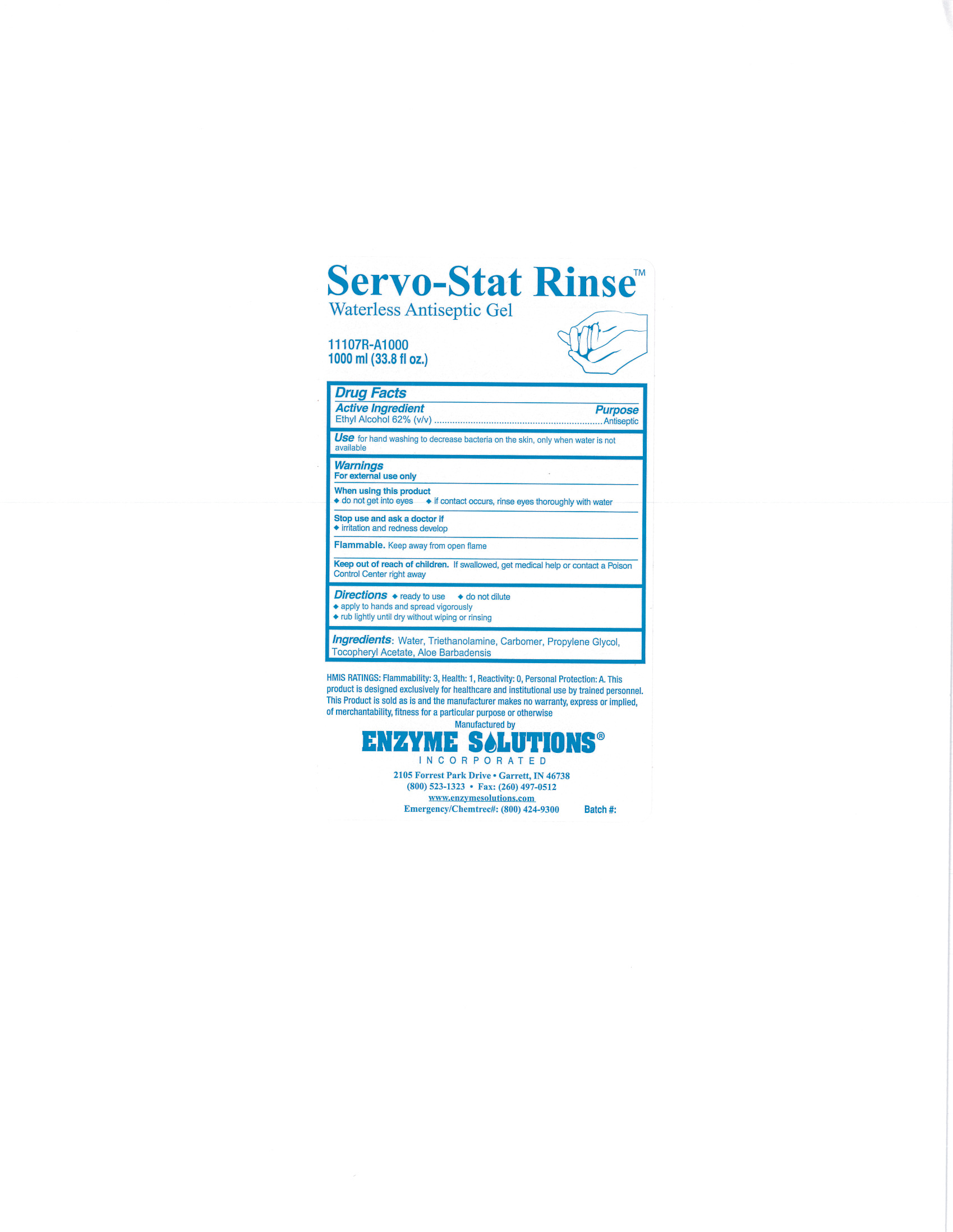 DRUG LABEL: Servo-Stat
NDC: 76378-015 | Form: GEL
Manufacturer: Enzyme Solutions, Inc.
Category: otc | Type: HUMAN OTC DRUG LABEL
Date: 20241126

ACTIVE INGREDIENTS: ALCOHOL 62 mL/100 mL
INACTIVE INGREDIENTS: WATER; TROLAMINE; CARBOMER HOMOPOLYMER TYPE C; PROPYLENE GLYCOL; .ALPHA.-TOCOPHEROL ACETATE, D-; ALOE VERA LEAF

Drug Facts 76378-015

Active Ingredient

Ethyl Alcohol 62% (v/v)

Purpose

Antiseptic

Use

for hand washing to decrease bacteria on the skin, only when water is not available

Warnings

For external use only

Flammable. Keep away from open flame

When using this product

do not get into eyes

if contact occurs, rinse eyes thoroughly with water

Stop use and ask a doctor if

irritation and redness develop

Keep out of reach of children.

If swallowed, get medical help or contact a Poison Control Center right away

Directions

ready to use

do not dilute

apply to hands and spread vigorously

rub lightly until dry without wiping or rinsing

INACTIVE INGREDIENT

Ingredients:

Water, Triethanolamine, Carbomer, Propylene Glycol, Tocopheryl Acetate, Aloe Barbadensis

PACKAGE LABEL

Servo-Stat Rinse

Waterless Antiseptic Gel

11107R-A1000

1000 ml (33.8 fl oz.)